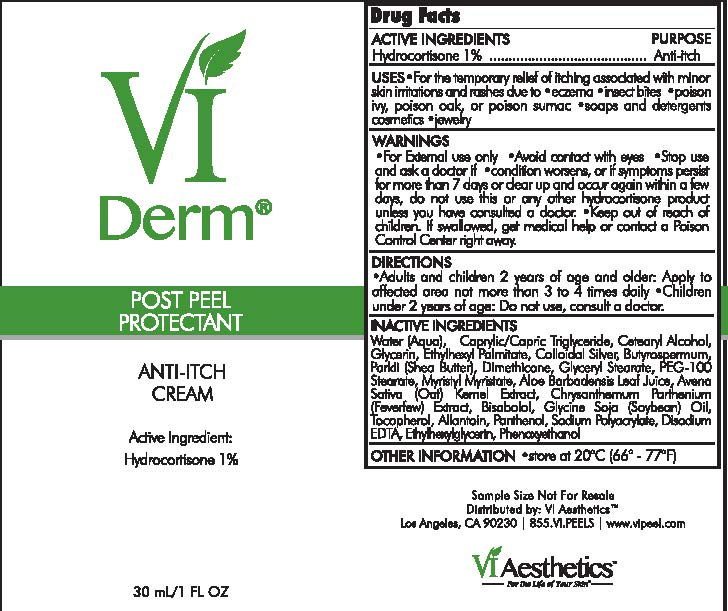 DRUG LABEL: Post peel Protectant
NDC: 70484-006 | Form: CREAM
Manufacturer: Vi Medical Products Inc.
Category: otc | Type: HUMAN OTC DRUG LABEL
Date: 20200115

ACTIVE INGREDIENTS: HYDROCORTISONE 7.5 g/100 mL
INACTIVE INGREDIENTS: WATER; CYCLOMETHICONE 5; DIMETHICONE/VINYL DIMETHICONE CROSSPOLYMER (SOFT PARTICLE); ALOE VERA LEAF; GLYCERIN; CETOSTEARYL ALCOHOL; POLYOXYL 20 CETOSTEARYL ETHER; MEDIUM-CHAIN TRIGLYCERIDES; CETYL ALCOHOL; AMMONIUM ACRYLOYLDIMETHYLTAURATE/VP COPOLYMER; OAT; TANACETUM PARTHENIUM; .ALPHA.-TOCOPHEROL ACETATE; ALLANTOIN; ETHYLHEXYLGLYCERIN; PHENOXYETHANOL

Post Peel Protectant Anti-Itch Cream

Active Ingredients Purpose

Hydrocortisone 1% ................. Anti-itch

Uses

- For the temporary relief of of itching associated with minor skin irritations and rashes due to
- Eczema
- insect bites
- poison ivy, poison oak, poison sumac
- soaps and detergents cosmetics
- jewelry

- Keep out of reach of children. If swallowed, get medial help or contact a Poison Control Center rigth away

Stop use and ask a doctor

if condition worsens, or if symptoms persist for more than 7 day or clear up and occur again within a few days, do not use this or any other hydrocortisone products unless you hav consulted a doctor.

Warnings

- For external use only
- Avoid Contact with eyes

Directions

- Adults and children under 2 years of age and older: Appyl to affected area not more than 3 to 4 times daily
- Children under 2 years of age: Do not use, consult a doctor

Inactive Ingredients

Water (Aqua), Cyclopentasiloxane, Demthicone/Vinyl Dimethicone Crosspolymer, Aloe Barbadensis Leaf Juice, Glycerin, Cetearyl Alcohol, Ceteareth-20, Caprylic/Capric Triglyceride, Cetyl Alcohol, Ammonium Acryloyldimethyltaurate/VP Copolymer, Avena Sativa (Oat) Kernel Extract, Chrysanthemum Pathenium (Feverfew) Extract, Tocophoneryl Acetate, Allantoint, Ethylhexylglycerin, Phenoxyethanol

PACKAGE LABEL

Vitality Institute

Skin Care System

Post Peel Protectant

Anti-itch Cream

30 mL/1 FL OZ